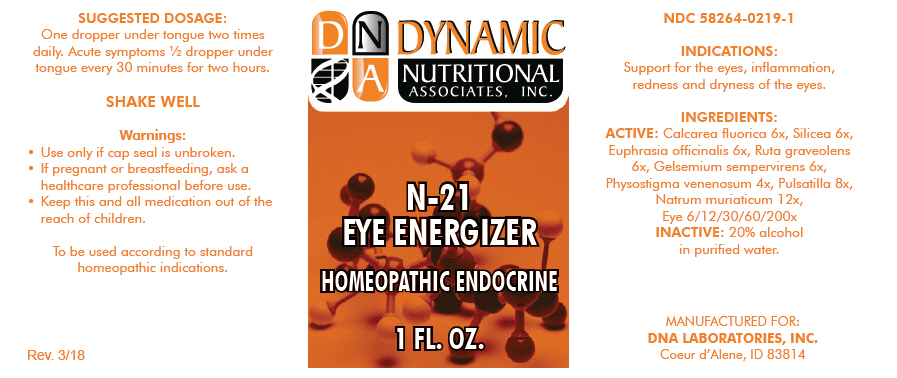 DRUG LABEL: N-21
NDC: 58264-0219 | Form: SOLUTION
Manufacturer: DNA Labs, Inc.
Category: homeopathic | Type: HUMAN OTC DRUG LABEL
Date: 20250109

ACTIVE INGREDIENTS: CALCIUM FLUORIDE 6 [hp_X]/1 mL; SILICON DIOXIDE 6 [hp_X]/1 mL; EUPHRASIA STRICTA 6 [hp_X]/1 mL; RUTA GRAVEOLENS WHOLE 6 [hp_X]/1 mL; GELSEMIUM SEMPERVIRENS WHOLE 6 [hp_X]/1 mL; PHYSOSTIGMA VENENOSUM WHOLE 4 [hp_X]/1 mL; ANEMONE PULSATILLA 8 [hp_X]/1 mL; SODIUM CHLORIDE 12 [hp_X]/1 mL; SUS SCROFA EYE 200 [hp_X]/1 mL
INACTIVE INGREDIENTS: ALCOHOL; WATER

N-21

NDC 58264-0219-1

INDICATIONS

PURPOSE

Support for the eyes, inflammation, redness and dryness of the eyes.

INGREDIENTS

ACTIVE

Calcarea fluorica 6x, Silicea 6x, Euphrasia officinalis 6x, Ruta graveolens 6x, Gelsemium sempervirens 6x, Physostigma venenosum 4x, Pulsatilla 8x, Natrum muriaticum 12x, Eye 6/12/30/60/200x

INACTIVE

20% alcohol in purified water.

SUGGESTED DOSAGE

One dropper under tongue two times daily. Acute symptoms ½ dropper under tongue every 30 minutes for two hours.

STORAGE AND HANDLING

SHAKE WELL

Warnings

- Use only if cap seal is unbroken.

PREGNANCY OR BREAST FEEDING

- If pregnant or breastfeeding, ask a healthcare professional before use.

KEEP OUT OF REACH OF CHILDREN

- Keep this and all medication out of the reach of children.

To be used according to standard homeopathic indications.

PRINCIPAL DISPLAY PANEL - 1 FL. OZ. Bottle Label

DYNAMIC
NUTRITIONAL
ASSOCIATES, INC.

N-21

EYE ENERGIZER

HOMEOPATHIC ENDOCRINE

1 FL. OZ.